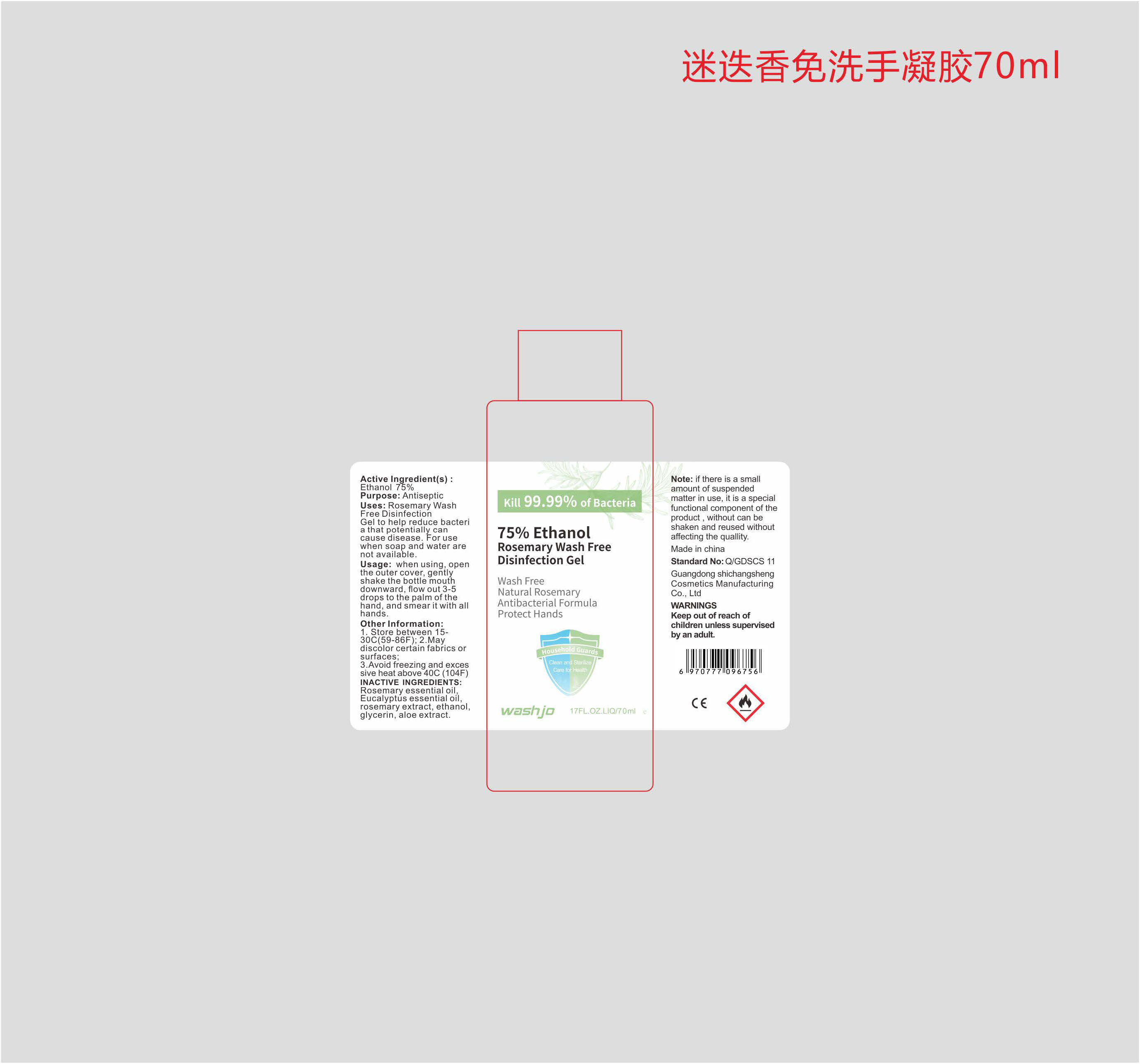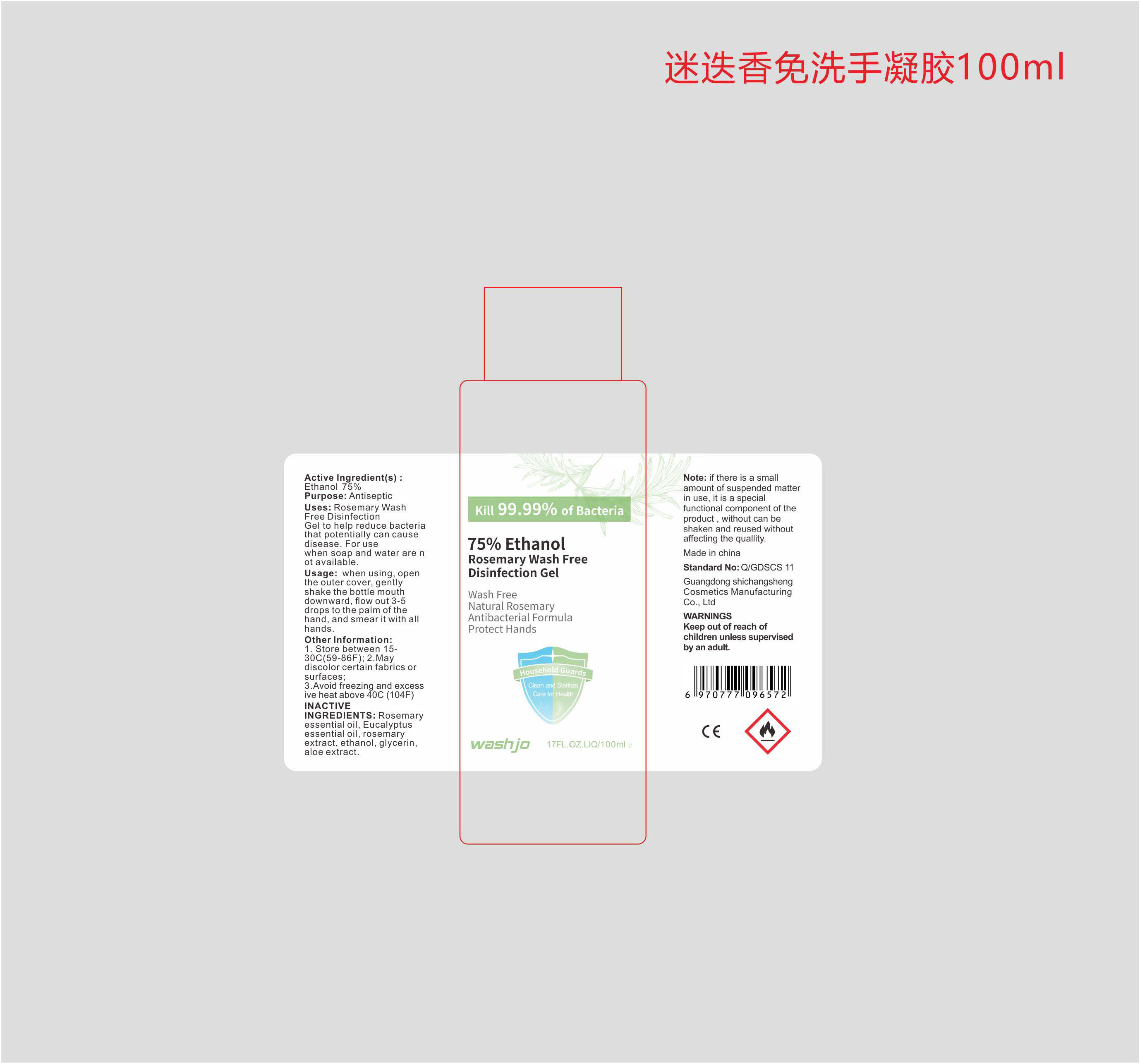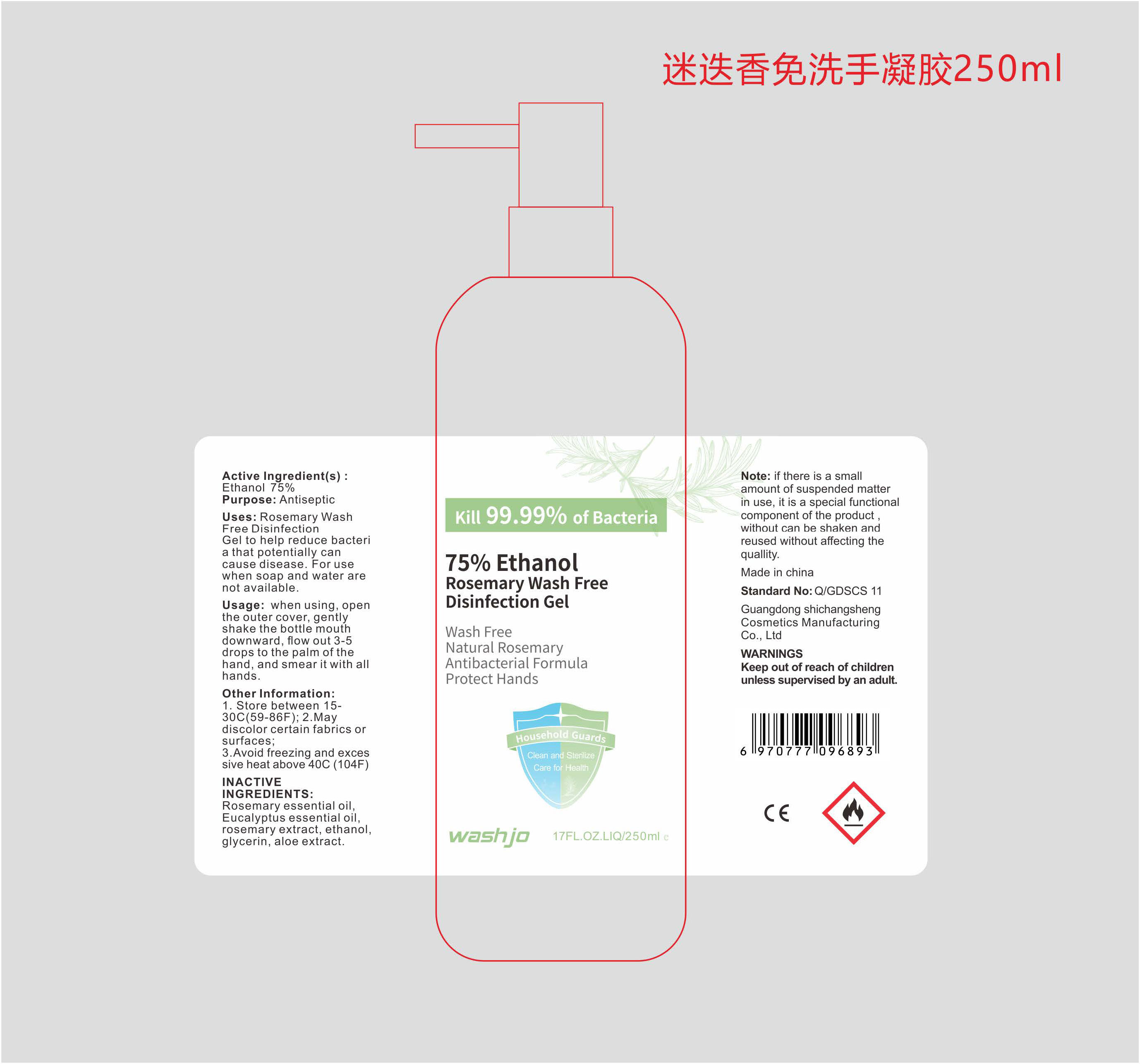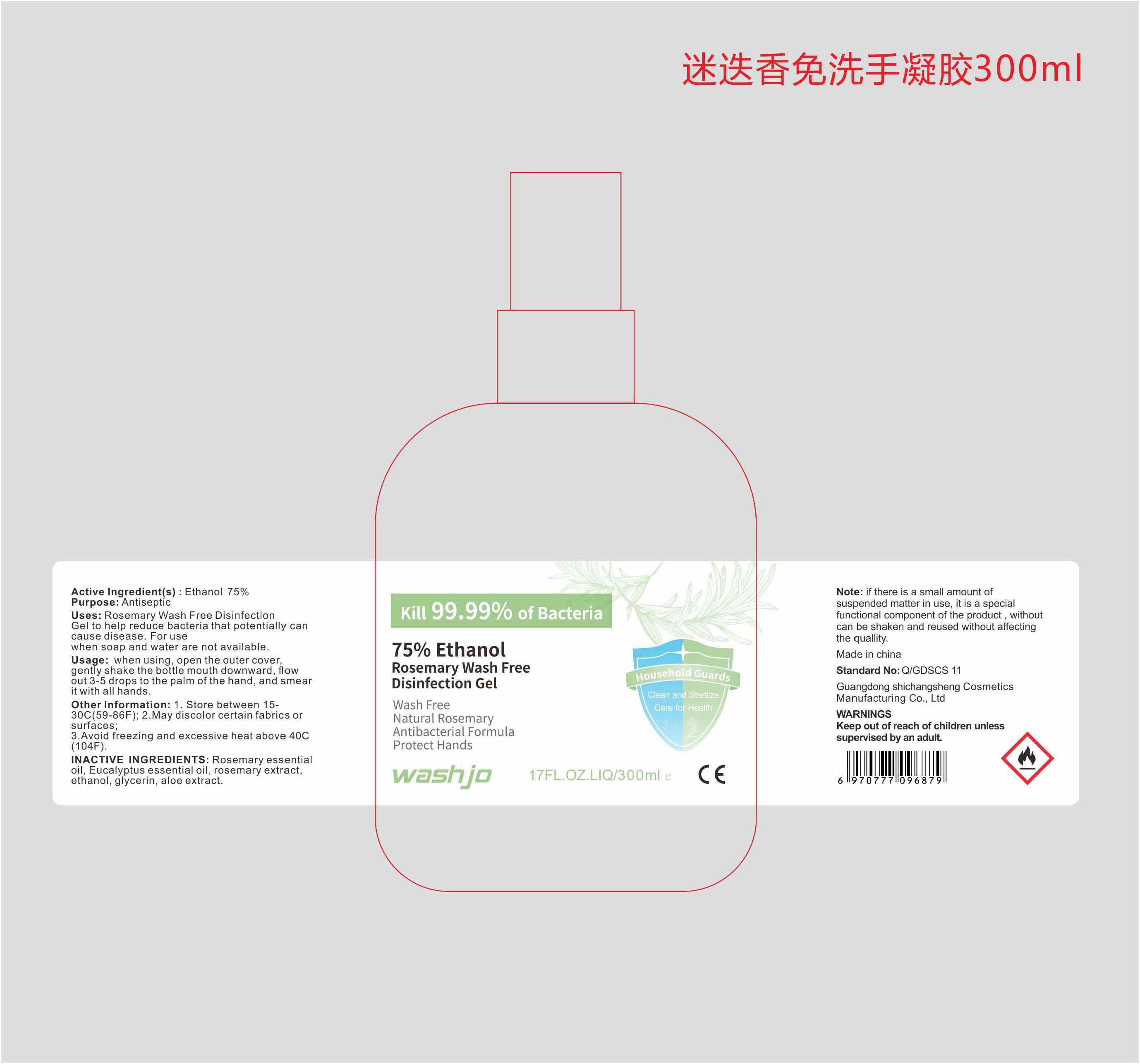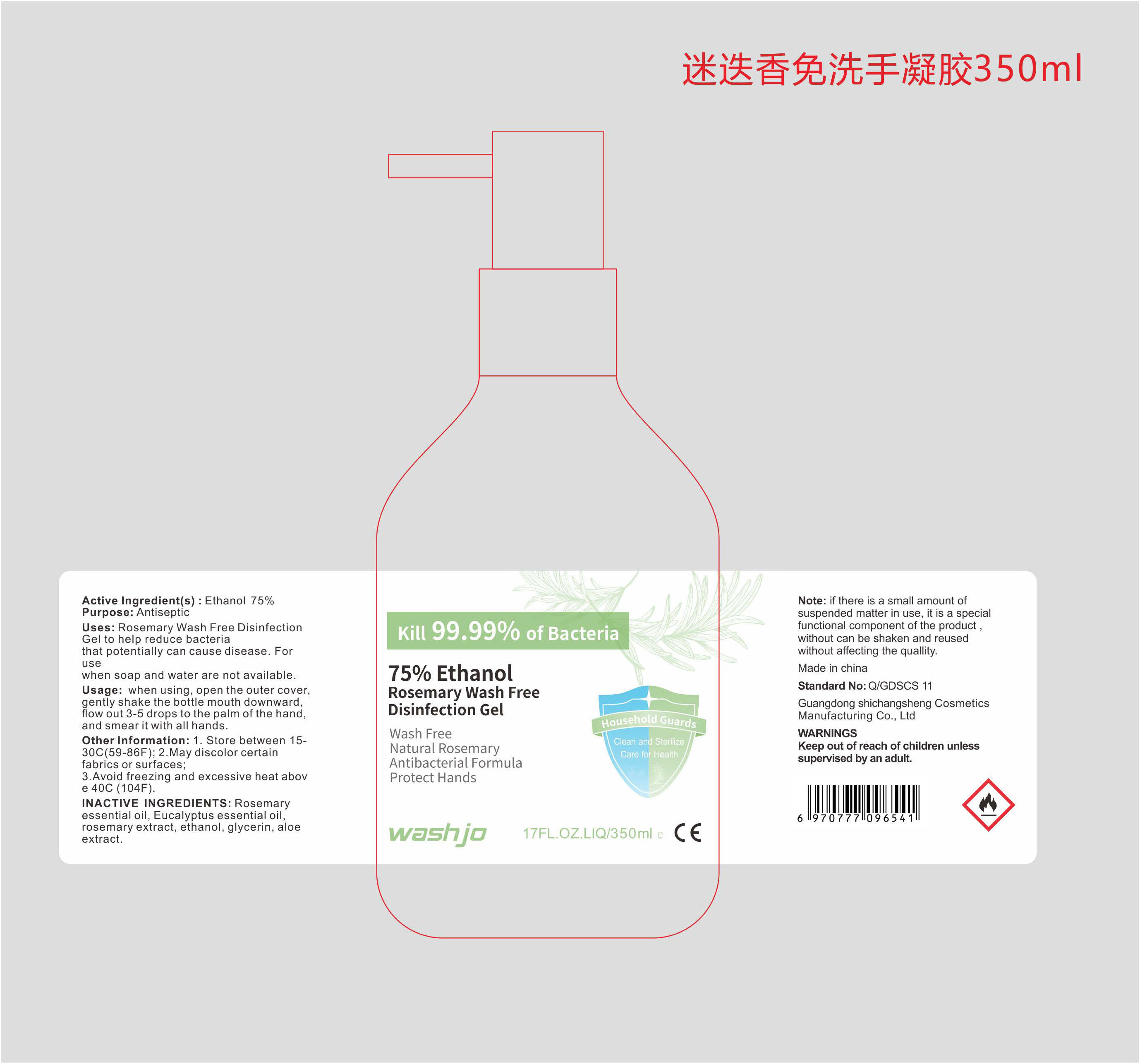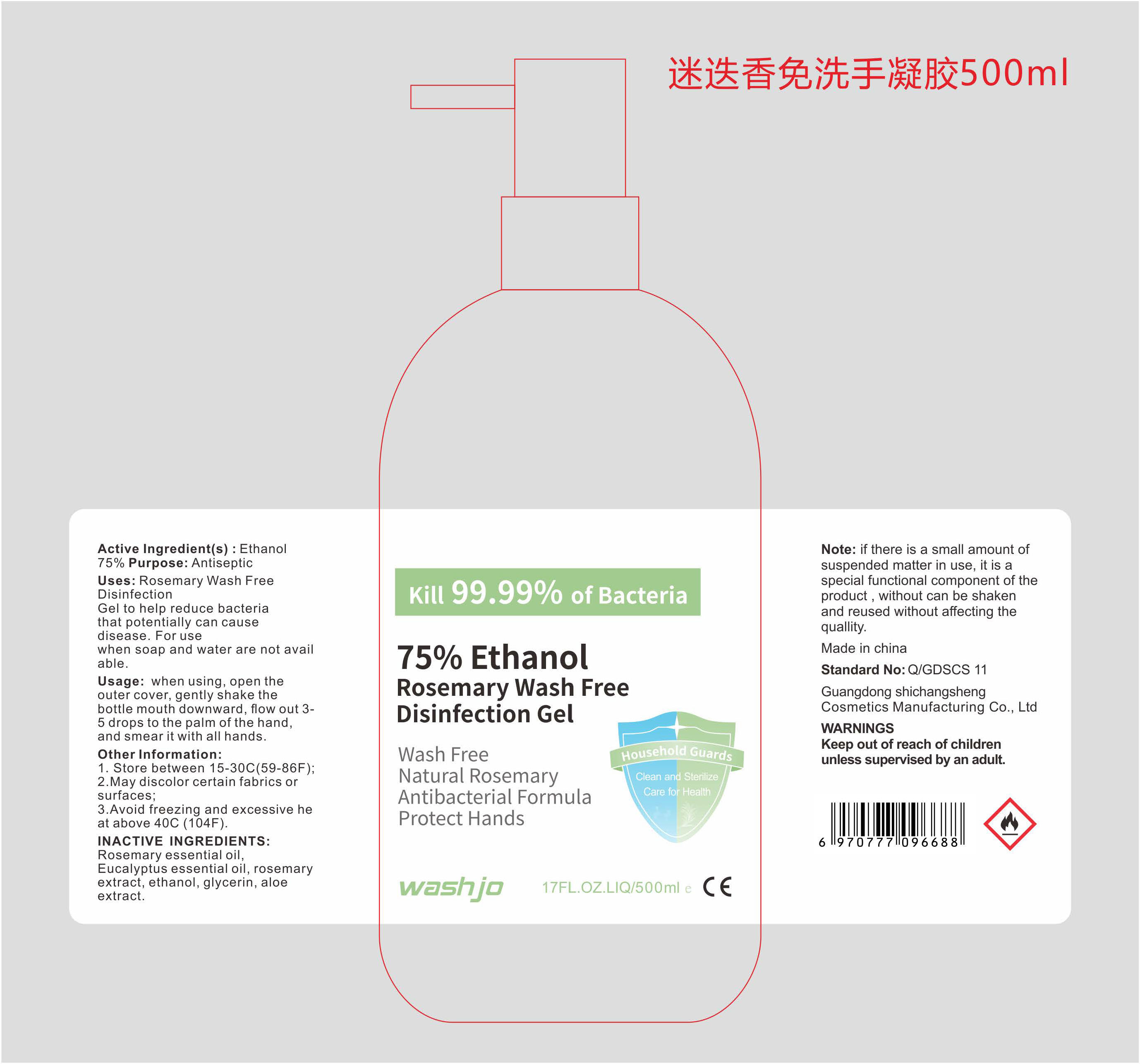 DRUG LABEL: WashJo Rosemary free hand disinfectant
NDC: 75824-005 | Form: GEL
Manufacturer: Shenzhen Flowerset Cosmetics Co., Ltd
Category: otc | Type: HUMAN OTC DRUG LABEL
Date: 20200422

ACTIVE INGREDIENTS: ALCOHOL 75 mL/100 mL
INACTIVE INGREDIENTS: GLYCERIN; ALOE

Rosemary Wash Free Disinfection Gel

Active Ingredient(s)

Ethanol 75%

Purpose

Antiseptic

Uses

Rosemary Wash Free Disinfection Gel to help reduce bacteria that potentially can cause disease.For use when soap and water are

not available.

WARNINGS

Keep out of reach of children unless supervised by an adult.

Other information

1.Store between 15-30C(59-86F) ;

2.May discolor certain fabrics or surfaces;

3.Avoid freezing and excessive heat above 40C(104F)

INACTIVE INGREDIENTS

Rosemary essential oil,Eucalyptus essential oil, rosemary extract,ethanol,glycerin, aloe extract.